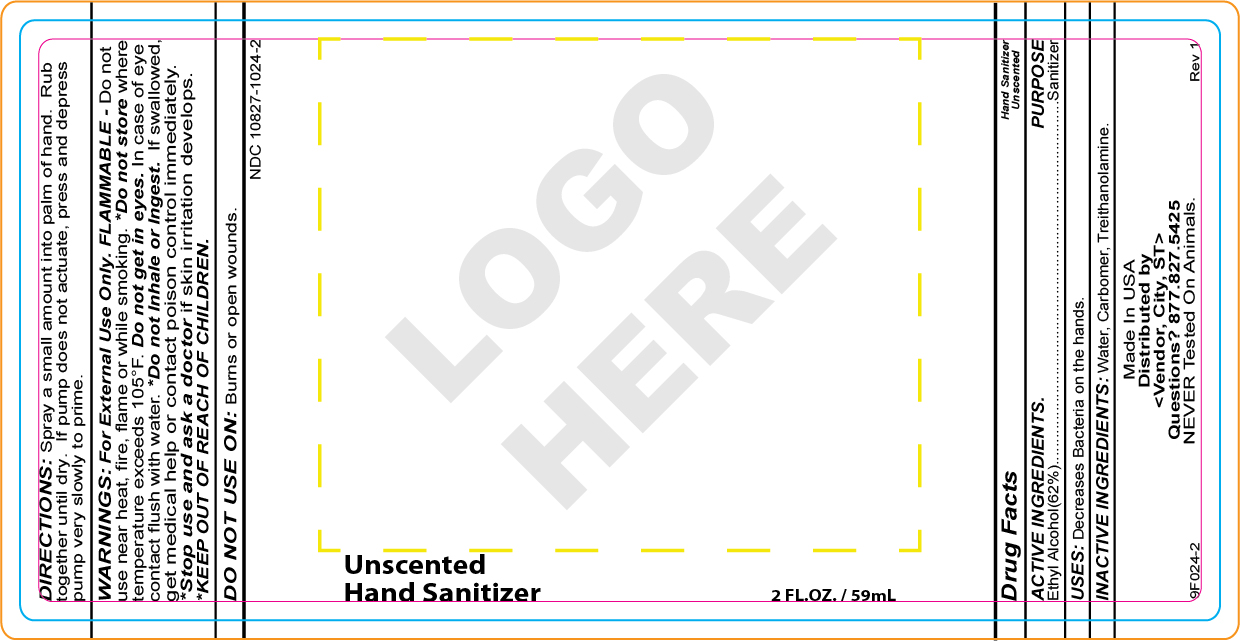 DRUG LABEL: YMLABS
NDC: 10827-1024 | Form: SPRAY
Manufacturer: Yusef Manufacturing Laboratories
Category: otc | Type: HUMAN OTC DRUG LABEL
Date: 20220203

ACTIVE INGREDIENTS: ALCOHOL 62 g/100 g
INACTIVE INGREDIENTS: WATER; CARBOMER HOMOPOLYMER TYPE A; TROLAMINE

YMlabs Spray Hand Sanitizer Unscented

INDICATIONS AND USAGE

DIRECTIONS: Spray a small amount into palm of hand. Rub
together until dry. If pump does not actuate, press and depress pump very slowly to prime.

WARNINGS

WARNINGS: For External Use Only. FLAMMABLE - Do not use near
heat, fire, flame or while smoking. *Do not store where temperature exceeds
105°F. Do not get in eyes. In case of eye contact flush with water. *Do not
Inhale or Ingest. If swallowed, get medical help or contact poison control
immediately. *Stop use and ask a doctor if skin irritation develops.
*KEEP OUT OF REACH OF CHILDREN.

*KEEP OUT OF REACH OF CHILDREN.

Drug Facts

Active ingredients Purpose

Ethyl Alcohol (62%).......Sanitizer

PURPOSE

USES: Decreases Bacteria on the hands.

INACTIVE INGREDIENTS: Water, Carbomer, Treithanolamine.

Made In USA
Distributed by
<Vendor, City, ST>
Questions? 877.827.5425
NEVER Tested On Animals.